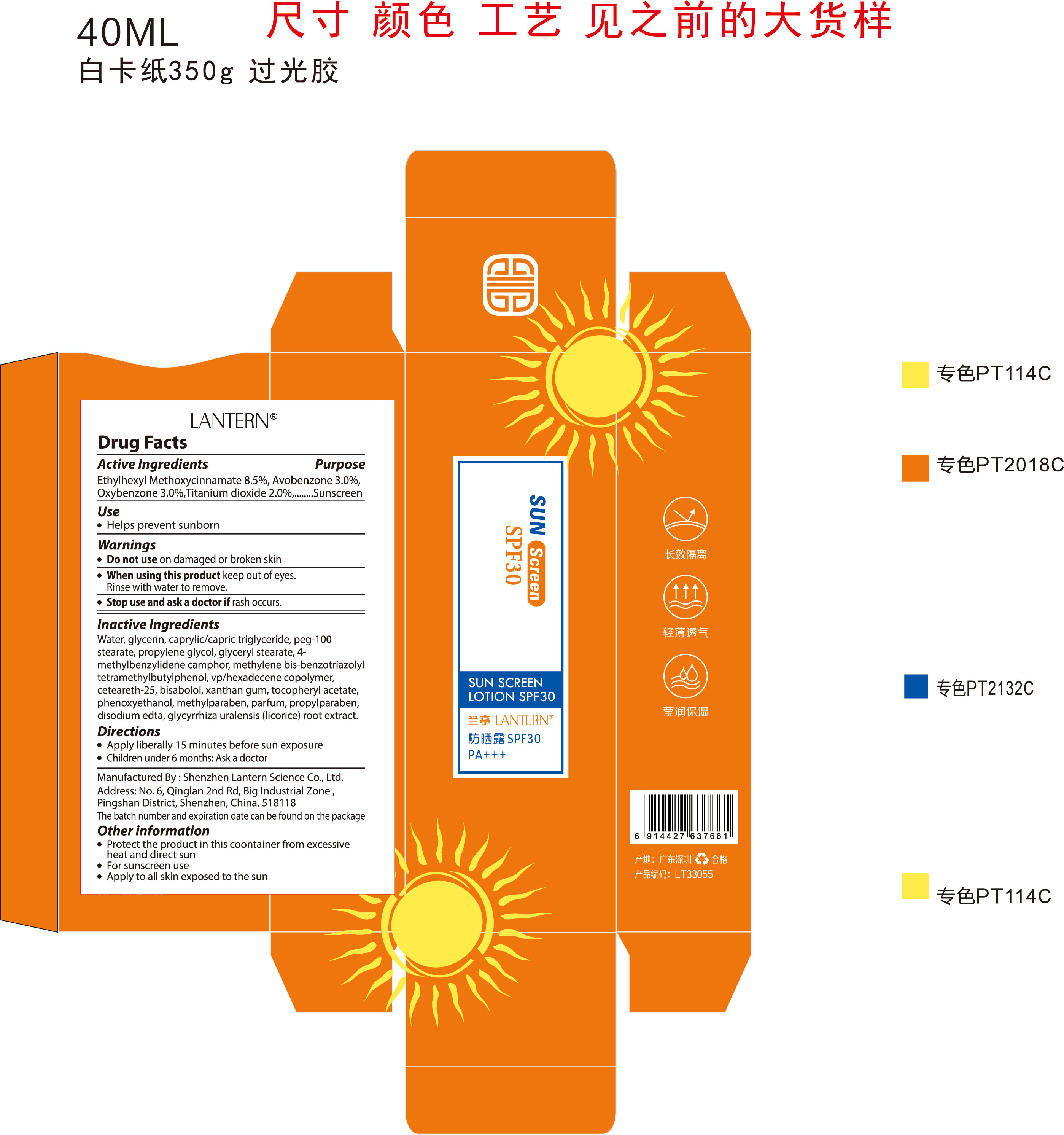 DRUG LABEL: SUN SCREENLOTION SPF30
NDC: 54860-417 | Form: LOTION
Manufacturer: Shenzhen Lantern Scicence Co.,Ltd.
Category: otc | Type: HUMAN OTC DRUG LABEL
Date: 20231018

ACTIVE INGREDIENTS: OCTINOXATE 8.5 g/100 mL; OXYBENZONE 3 g/100 mL; AVOBENZONE 3 g/100 mL
INACTIVE INGREDIENTS: GLYCYRRHIZA URALENSIS; CAPRYLIC/CAPRIC/PALMITIC/STEARIC TRIGLYCERIDE; PEG-100 STEARATE; GLYCERIN; GLYCERYL STEARATE SE; DIPROPYLENE GLYCOL; ENZACAMENE; VINYLPYRROLIDONE/HEXADECENE COPOLYMER; CETEARETH-25; .ALPHA.-BISABOLOL, (+/-)-; XANTHAN GUM; PHENOXYETHANOL; METHYLPARABEN; PROPYLPARABEN; WATER; DISODIUM EDTA-COPPER

SUN SCREENLOTION SPF30

Active Ingredient

ETHYLHEXYL METHOXYCINNAMATE：8.5%

Avobenzone：3.0%

Titanium dioxide：3.0%

Sunscreen

Inactive ingredients

AQUA, METHYLENE BIS-BENZOTRIAZOLYL TETRAMETHYLBUTYLPHE NOL, AQUA, DECYL GLUCOSIDE, PROPYLENE GLYCOL, XANTHAN GUM, GLYCERIN, DIETHYLAMINO HYDROXYBENZOYL HEXYL BENZOATE, BIS-ETHYLHEXYLOXYPHENOL METHOXYPHENYL TRIAZINE, ETHYLHEXYL TRIAZONE, DIMETHICONE, PEG-20 METHYL GLUCOSE SESQUISTEARATE, AMMONIUM ACRYLOYLDIMETHYLTAURATE/VP COPOLYMER, METHYL GLUCOSE SESQUISTEARATE, PHENOXYETHANOL, TOCOPHERYL ACETATE, PARFUM, MENTHOL, METHYLPARABEN, BISABOLOL, ALLANTOIN, PROPYLPARABEN, DISODIUM EDTA, SPIRULINA PLATENSIS EXTRACT, SODIUM HYALURONATE.

Directions

Apply liberaaly 15 minutes before sun exposure.

Children under 6 months; Ask a doctor.

When using this product

keep out of eyes. In case of contact with eyes, flush thoroughly with water.

Do not inhale or ingest.

Avoid contact with broken skin.

Other information

Do not store above 105F.

May discolor some fabrics.

Harmful to wood finishes and plastics.

When using this product

Keep out of eyes,Rinse with water to remove.

Purpose

Sunscreen

Stop use and ask a doctor

if rash occurs.

Do not use

on danaged or broken skin.

Other information

Protect the product in this container from excessive heat and direct sun.

For sunscreen use

Apply to all skin exposed to the sun

Limit time in the sun,especially from 10 a.m.-2 p.m.

Wear long-s;eeved shirts,pants,hats,and sunglasses.

Warnings

For external use only

DOSAGE & ADMINISTRATION SECTION

Emulsion，Apply generously 15 minutes before sun exposure

Reapply at least every 2 hours

Keep out of reach of children.

If swallowed, get medical help or contact a Poison Control Center right away.

Packaging